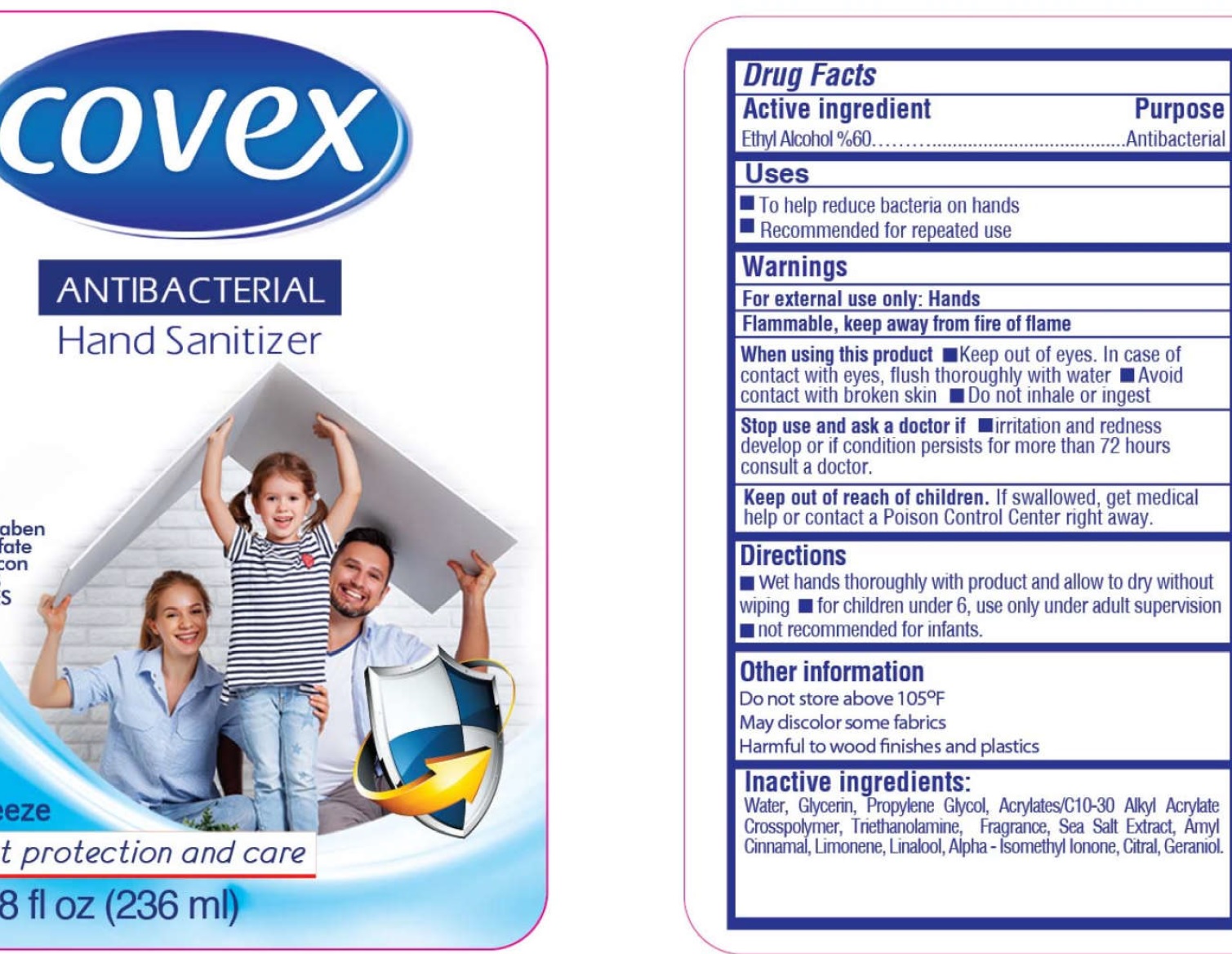 DRUG LABEL: Covex Antibacterial Hand Sanitizer, COOL BREEZE
NDC: 51209-012 | Form: GEL
Manufacturer: DALAN KIMYA ENDUSTRI ANONIM SIRKETI
Category: otc | Type: HUMAN OTC DRUG LABEL
Date: 20260122

ACTIVE INGREDIENTS: ALCOHOL 0.6 mL/1 mL
INACTIVE INGREDIENTS: WATER; GLYCERIN; PROPYLENE GLYCOL; CARBOMER INTERPOLYMER TYPE A (ALLYL SUCROSE CROSSLINKED); TROLAMINE; .ALPHA.-AMYLCINNAMALDEHYDE; LIMONENE, (+)-; LINALOOL, (+/-)-; ISOMETHYL-.ALPHA.-IONONE; CITRAL; GERANIOL

Covex Antibacterial Hand Sanitizer, COOL BREEZE

Active ingredients

Ethyl Alcohol %60

Purpose

Antibacterial

Uses

- To help reduce bacteria on hands
- Recommended for repeated use

Warnings

For external use only: Hands

Flammable, keep away from fire of flame

When using this product.

- Keep out of eyes. In case of contact with eyes, flush thoroughly with water.
- Avoid contact with broken skin
- Do not inhale or ingest

Stop use and ask a doctor if

- irritation and redness develop or if condition persists for more than 72 hours consult a doctor.

Keep out of reach of children.

If swallowed, get medical help or contact a Poison Control Center right away.

Directions

- Wet hands thoroughly with product and allow to dry without wiping - for children under 6, use only under adult supervision - not recommended for infants.

Other information

Do not store above 105°F

May discolor some fabrics

Harmful to wood finishes and plastics

Inactive ingredients:

Water, Glycerin, Propylene Glycol, Acrylates/C10-30 Alkyl Acrylate Crosspolymer, Triethanolamine, Fragrance, Sea Salt Extract, Amyl Cinnamal, Limonene, Linalool, Alpha-Isomethyl Ionone, Citral, Geraniol